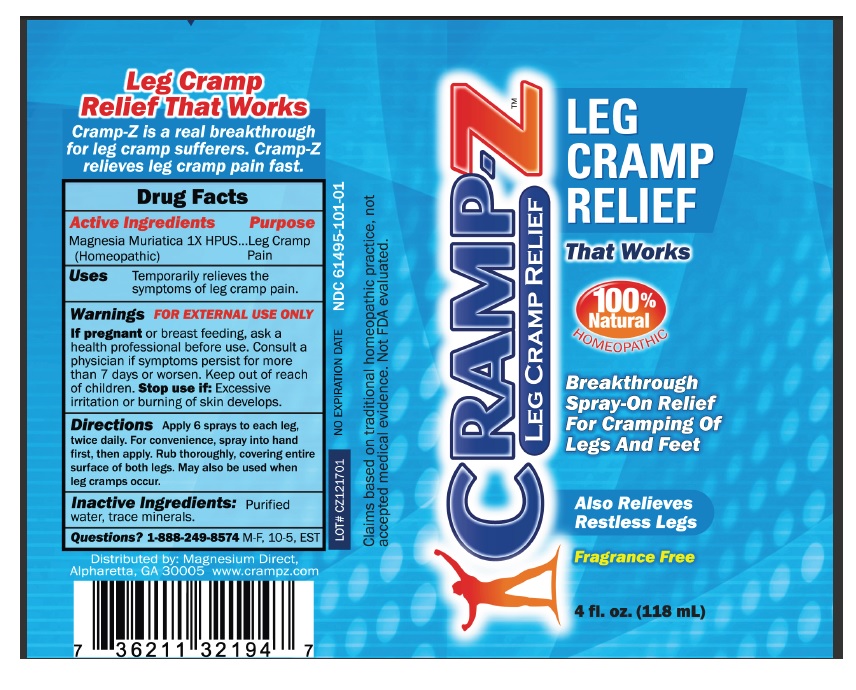 DRUG LABEL: Cramp-Z
NDC: 61495-101 | Form: SPRAY
Manufacturer: MAGNESIUM DIRECT INC.
Category: homeopathic | Type: HUMAN OTC DRUG LABEL
Date: 20190103

ACTIVE INGREDIENTS: MAGNESIUM CHLORIDE 1 [hp_X]/1 mL
INACTIVE INGREDIENTS: WATER

Cramp-Z

Active ingredients

Magnesia Muriatica 1X HPUS

(Homeopathic)

Purpose

Leg Cramp Pain

Keep out of reach of children

Uses

Temporarily relieves the symptoms of leg cramp pain

Warnings FOR EXTERNAL USE ONLY.

If pregnant or breast feeding, ask a health professional before use. Consult a physician if symptoms persist for more than 7 days or worsen.

Stop use if: Excessive irritation or burning of skin develops.

DOSAGE AND ADMINISTRATION

Directions Apply 6 sprays to each leg twice daily. For convenience, spray in to hand first, then apply. Rub thoroughly, covering entire surface of both legs. May also be used when leg cramps occur.

Inactive ingredients: Purifiedwater, trace minerals.

QUESTIONS

Questions? 1-888-249-8574 M-F, 10-5, EST